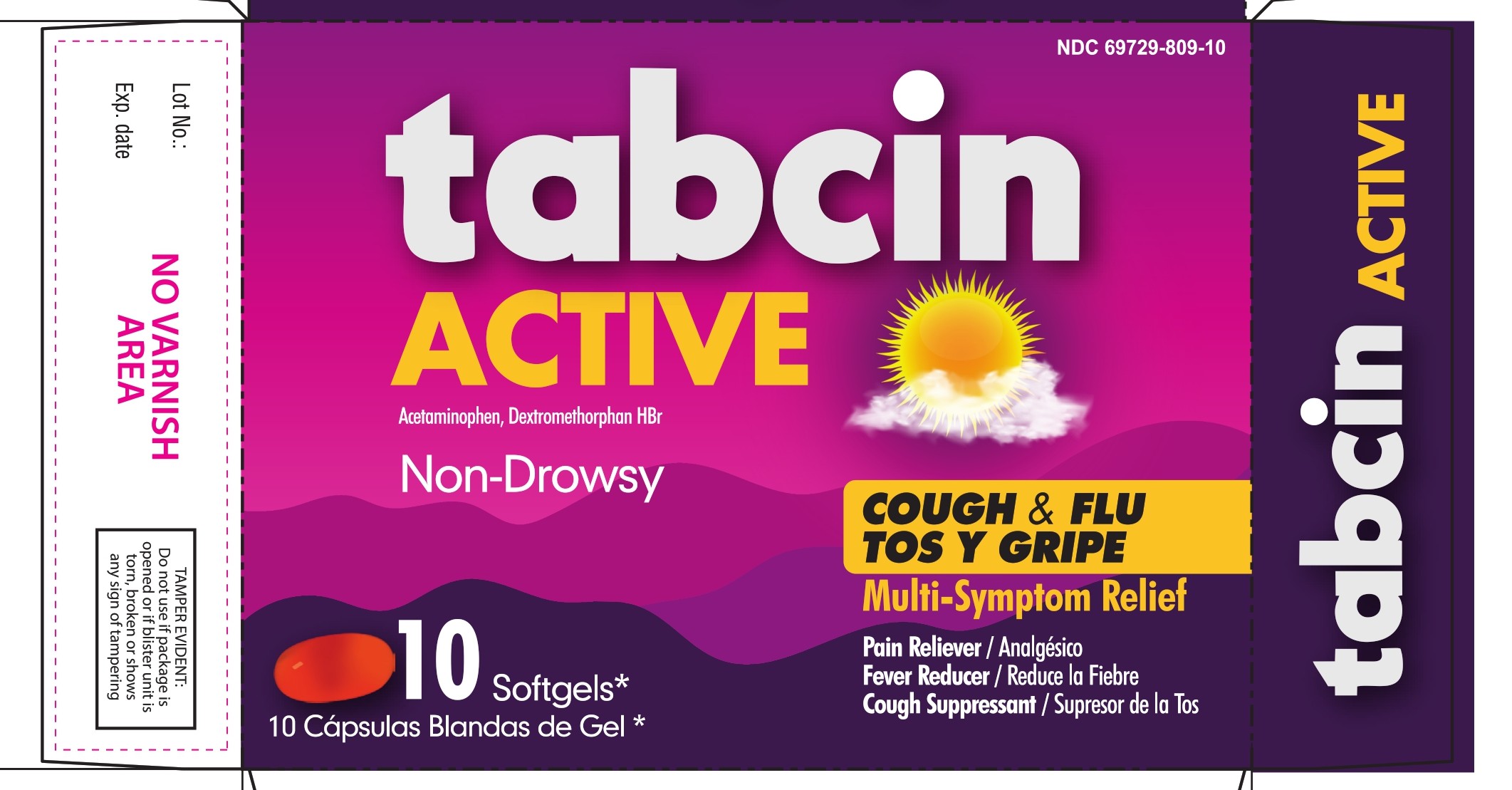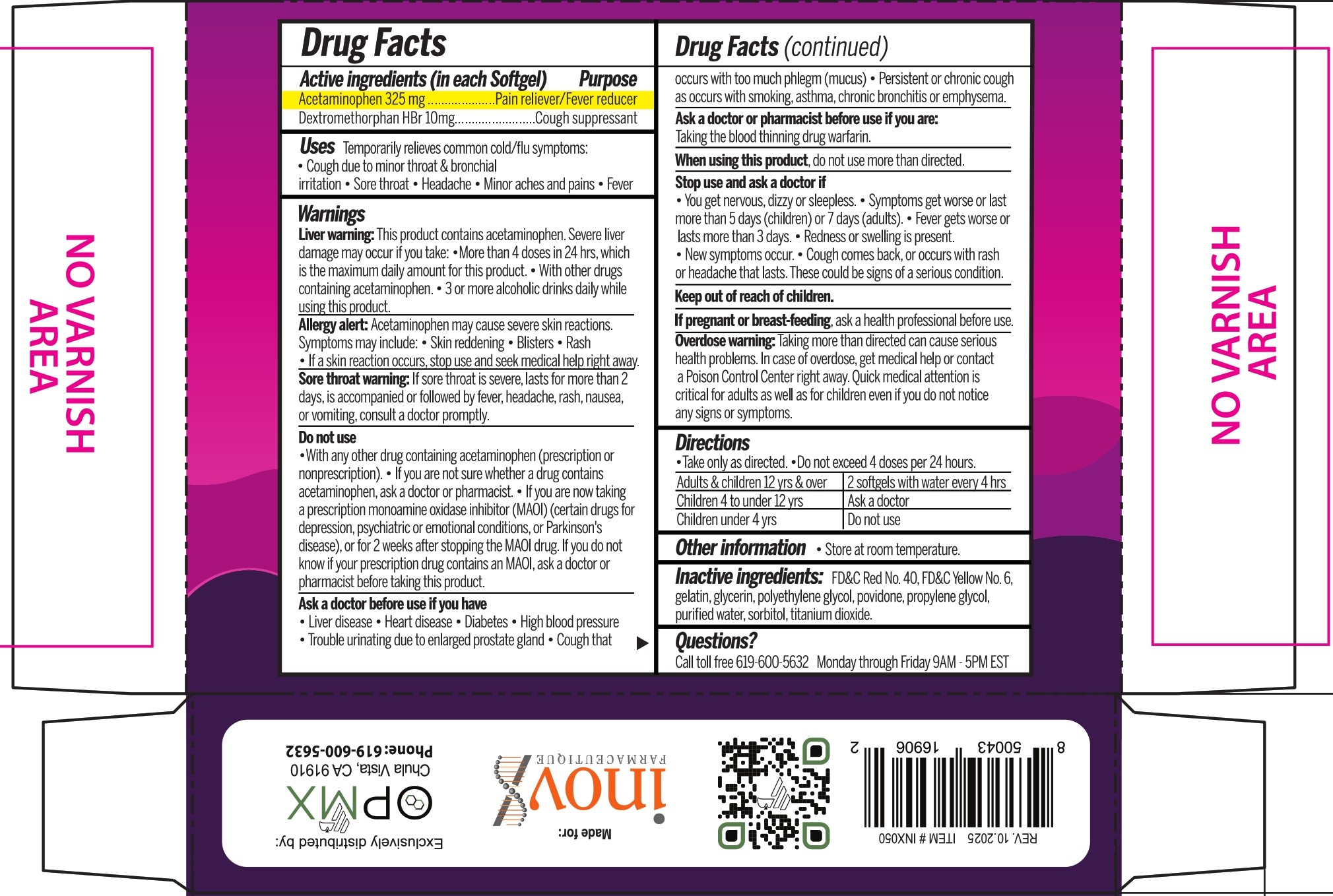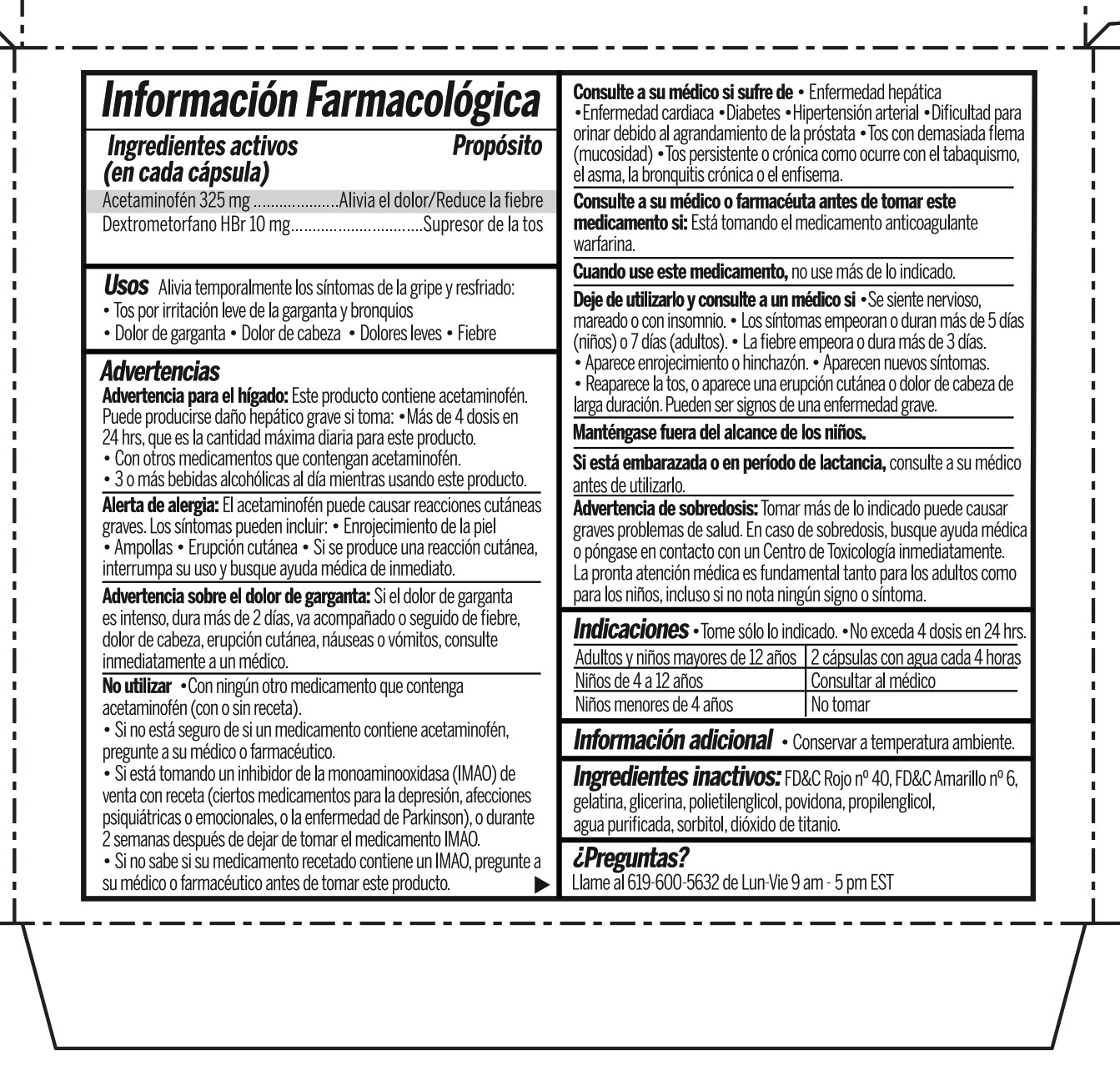 DRUG LABEL: tabcin ACTIVE
NDC: 69729-809 | Form: CAPSULE, LIQUID FILLED
Manufacturer: OPMX LLC.
Category: otc | Type: HUMAN OTC DRUG LABEL
Date: 20260130

ACTIVE INGREDIENTS: DEXTROMETHORPHAN HYDROBROMIDE 10 mg/1 1; ACETAMINOPHEN 325 mg/1 1
INACTIVE INGREDIENTS: FD&C YELLOW NO. 6; FD&C RED NO. 40; GELATIN; GLYCERIN; POLYETHYLENE GLYCOL, UNSPECIFIED; POVIDONE; PROPYLENE GLYCOL; WATER; SORBITOL; TITANIUM DIOXIDE

Tabcin Active w/10 Softgel NUEVA FORMULA

Drug Facts

Active ingredients (in each Softgel)

- Acetaminophen 325 mg
- Dextromethorphan HBr 10 mg

Purpose

- Pain reliever/ Fever reducer
- Cough suppressant

Uses

Temporarily relieves common cold/flu symptoms:

- Cough due to minor throat & bronchial irritation
- Sore throat
- Headache
- Minor aches & pains
- Fever

Warnings

Liver warning: This product contains acetaminophen. Severe liver damage may occur if you take:

- More than 4 doses in 24 hrs, which is the maximum daily amount for this product.
- With other drugs containing acetaminophen.
- 3 or more alcoholic drinks daily while using this product.

Allergy alert: Acetaminophen may cause severe skin reactions. Symtoms may include.

- Skin reddening
- Blisters
- Rash
- If a skin reaction occurs, stop use and seek medical help right away.

Sore throat warning: If sore throat is severe, lasts more than 2 days, is accompained or followed by fever, headache, rash, nausea, or vomiting, consult a doctor promplty.

Do not use

- With any other drug containing acetaminophen (prescription or nonprescription).
- If you are not sure whether a drug contains acetaminophen, ask a doctor or pharmacist.
- If you are now taking a prescription monoamine oxidase inhibitor (MAOI) (certain drugs for depression, psychiatric or emotional conditions, or Parkinson's disease), or for 2 weeks after stopping the MAOI drug. If you do not know if your prescription drug contains an MAOI, ask a doctor or pharmacist before taking this product.

Ask a doctor before use if you have

- Liver disease
- Heart disease
- Diabetes
- High blood pressure
- Trouble urinating due to enlarged prostate gland
- Cough that occurs with too much phlegm (mucus)
- Persistent or chronic cough as occurs with smoking, asthma, chronic bronchitis or emphysema.

Ask a doctor or pharmacist before use if you are:

Taking the blood thinning drug warfarin.

When using this product,

do not use more than directed.

Stop use and ask a doctor if

- You get nervous, dizzy or sleepless.
- Symptoms get worse or last more than 5 days (children) or 7 days (adults).
- Fever gets worse or lasts more than 3 days.
- Redness or swelling is present.
- New symtoms occur.
- Cough comes back, or occurs with rash or headache that lasts.

These could be signs of a serious condition.

Keep out of reach of children.

If pregnant or breast-feeding,

ask a health professional before use.

Overdose warning

Taking more than directed can cause serious health problems. In case of overdose, get medical help or contact a Poison Control Center right away. Quick medical attention is critical for adults as well for children even if you do not notice any signs or symptoms.

Directions

- Take only as directed.
- Do not exceed 4 doses per 24 hrs.

Adults & children 12 yrs & over | 2 softgels with water every 4 hrs
Children 4 to under 12 yrs | Ask a doctor
Children under 4 yrs | Do not use

Other information

- Store at room temperature

Inactive ingredients

FD&C Red No. 40, FD&C Yellow No. 6, gelatin, glycerin, polyethylene glycol, povidone, propylene glycol, purified water, sorbitol, titanium dioxide.

Questions?

Call to free 619-600-5632 Monday through Friday 9AM - 5PM EST

PRINCIPAL DISPLAY PANEL

NDC 69729-809-10

tabcin Active

Acetaminophen, Dextromethorphan HBr

Non-Drowsy

COUGH & FLU / TOS Y GRIPE

Multi-Symptom Relief

- Pain Reliever/ Analgésico
- Fever Reducer/ Reduce la Fiebre
- Cough Suppressant / Supresor de la Tos

10 Softgels* / 10 Cápsulas blandas de gel*